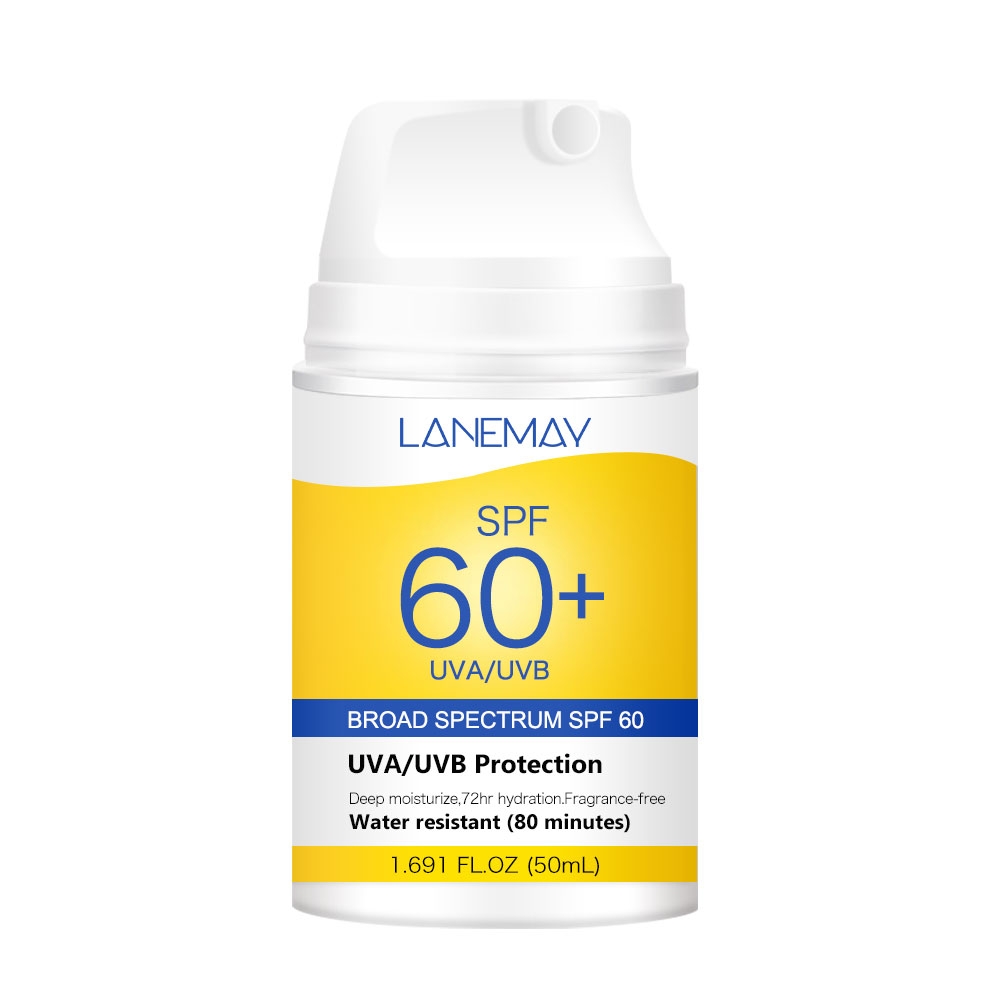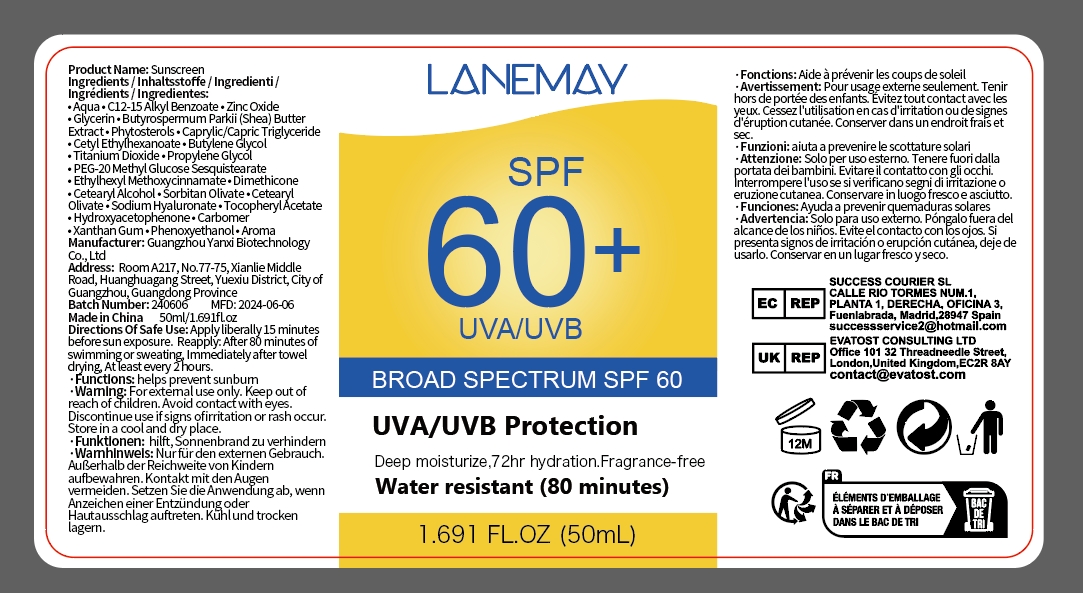 DRUG LABEL: Sunscreen
NDC: 84025-088 | Form: LOTION
Manufacturer: Guangzhou Yanxi Biotechnology Co.. Ltd
Category: otc | Type: HUMAN OTC DRUG LABEL
Date: 20240724

ACTIVE INGREDIENTS: ZINC OXIDE 5 mg/50 mL; GLYCERIN 3 mg/50 mL
INACTIVE INGREDIENTS: WATER

DOSAGE AND ADMINISTRATION

For dry, sun-damaged skin

WARNINGS

Keep out of children

INACTIVE INGREDIENT

Aqua

INDICATIONS AND USAGE

Moisturizes the skin and reduces sunburn.

Keep out of children

PURPOSE

Protects skin from sunburn